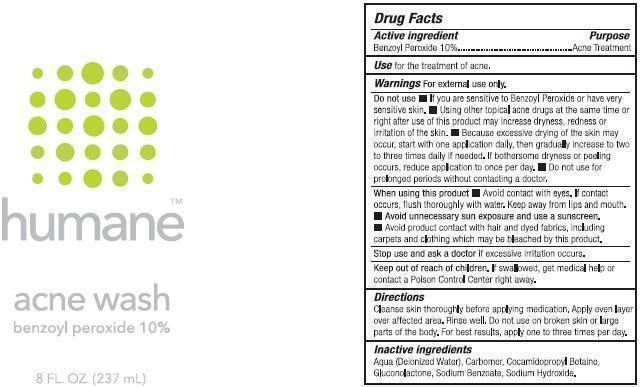 DRUG LABEL: humane acne wash
NDC: 69919-021 | Form: CREAM
Manufacturer: Banner 1 LLC
Category: otc | Type: HUMAN OTC DRUG LABEL
Date: 20250924

ACTIVE INGREDIENTS: BENZOYL PEROXIDE 100 mg/1 mL
INACTIVE INGREDIENTS: WATER; COCAMIDOPROPYL BETAINE; GLUCONOLACTONE; SODIUM BENZOATE; SODIUM HYDROXIDE

humane acne wash

Active Ingredient

Benzoyl Peroxide 10%

Purpose

Acne Treatment

use

for the treatment of acne.

Warnings

For external use only.

Do not use

- If you are sensitive to Benzoyl Peroxide or have very sensitive skin.
- Using other topical acne drugs at the same time or right after use of the product may increase dryness, redness or irritation of the skin.
- Because excessive drying of the skin may occur, start with one application daily, then gradually increase to two to three times daily if neede. If bothersome dryness or peeling occurs, reduce application to once per day.
- Do not use for prolonged periods without contacting a doctor.

When using this product

- Avoid contact with eyes. of contact occurs, flush thoroughly with water. Keep away from lips and mouth.
- Avoid unnecessary sun exposure and use a sunscreen.
- Avoid Product contact with hair and dyed fabrics, including carpets and clothing which may be bleached by this Product.

Stop use and ask a doctor

if excessive irritation occurs.

Keep out of reach of children.

If swallowed, get medical help or contact a Poison Control Center right away.

Directions

Cleanse Skin thoroughly before applying medication. Apply even layer over affected area. Rinse well. DO not use on broken skin or large parts of the body. For best results, apply one to three times per day.

Inactive ingredients

Aqua (Deionized Water), Carbomer, Cocamidopropyl Betaine, Gluconolactone, Sodium Benzoate, Sodium Hydroxide.